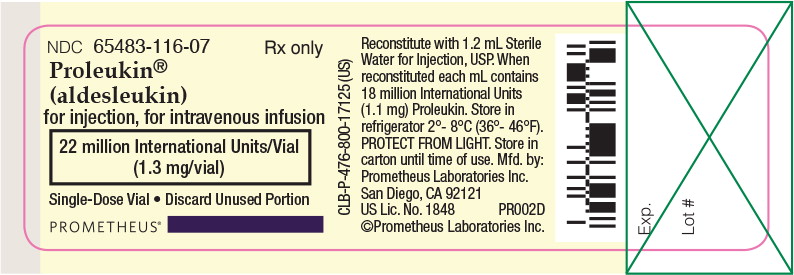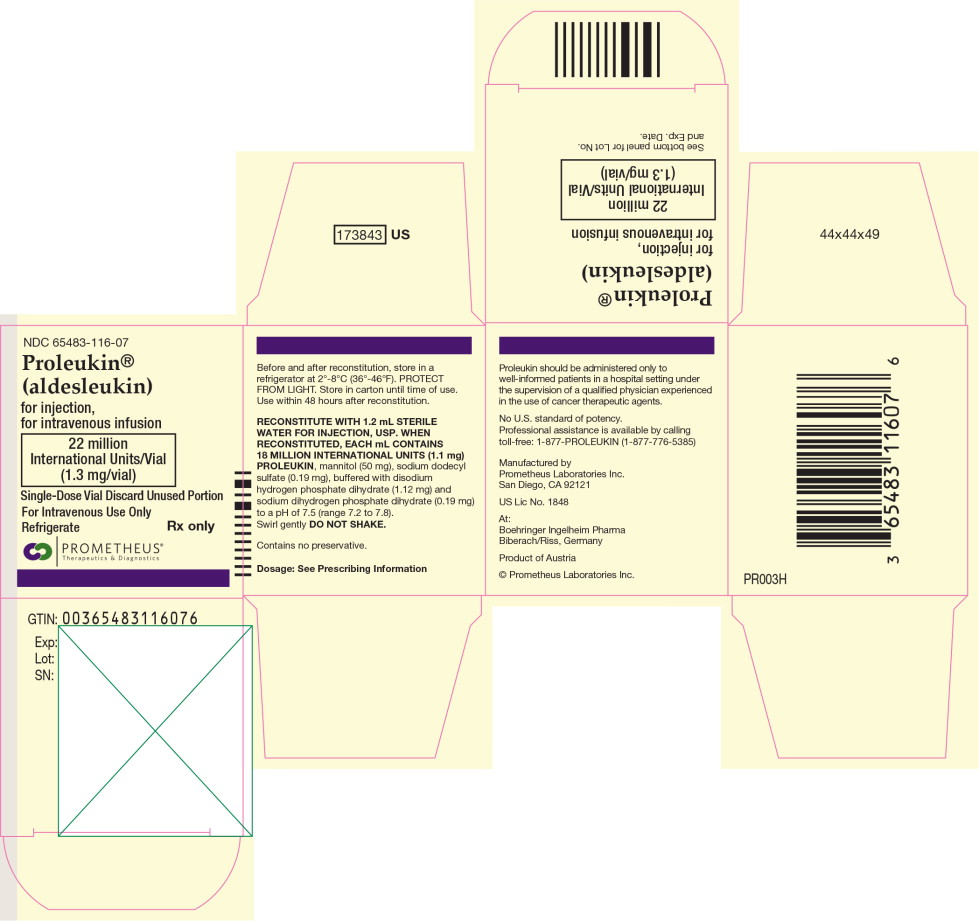 DRUG LABEL: Proleukin
NDC: 65483-116 | Form: INJECTION, POWDER, LYOPHILIZED, FOR SOLUTION
Manufacturer: Prometheus Laboratories Inc.
Category: prescription | Type: HUMAN PRESCRIPTION DRUG LABEL
Date: 20190523

ACTIVE INGREDIENTS: aldesleukin 1.1 mg/1 mL
INACTIVE INGREDIENTS: MANNITOL; SODIUM PHOSPHATE, MONOBASIC, UNSPECIFIED FORM; SODIUM LAURYL SULFATE; SODIUM PHOSPHATE, DIBASIC, UNSPECIFIED FORM; WATER

PROLEUKIN®

PROLEUKIN® (aldesleukin)

for injection, for intravenous infusion

Rx Only

WARNINGS

Therapy with Proleukin® (aldesleukin) should be restricted to patients with normal cardiac and pulmonary functions as defined by thallium stress testing and formal pulmonary function testing. Extreme caution should be used in patients with a normal thallium stress test and a normal pulmonary function test who have a history of cardiac or pulmonary disease.

Proleukin should be administered in a hospital setting under the supervision of a qualified physician experienced in the use of anticancer agents. An intensive care facility and specialists skilled in cardiopulmonary or intensive care medicine must be available.

Proleukin administration has been associated with capillary leak syndrome (CLS) which is characterized by a loss of vascular tone and extravasation of plasma proteins and fluid into the extravascular space. CLS results in hypotension and reduced organ perfusion which may be severe and can result in death. CLS may be associated with cardiac arrhythmias (supraventricular and ventricular), angina, myocardial infarction, respiratory insufficiency requiring intubation, gastrointestinal bleeding or infarction, renal insufficiency, edema, and mental status changes.

Proleukin treatment is associated with impaired neutrophil function (reduced chemotaxis) and with an increased risk of disseminated infection, including sepsis and bacterial endocarditis. Consequently, preexisting bacterial infections should be adequately treated prior to initiation of Proleukin therapy. Patients with indwelling central lines are particularly at risk for infection with gram positive microorganisms. Antibiotic prophylaxis with oxacillin, nafcillin, ciprofloxacin, or vancomycin has been associated with a reduced incidence of staphylococcal infections.

Proleukin administration should be withheld in patients developing moderate to severe lethargy or somnolence; continued administration may result in coma.

DESCRIPTION

Aldesleukin, a human recombinant interleukin-2 product, is a highly purified protein with a molecular weight of approximately 15,300 daltons. The chemical name is des-alanyl-1, serine-125 human interleukin-2. Aldesleukin, a lymphokine, is produced by recombinant DNA technology using a genetically engineered E. coli strain containing an analog of the human interleukin-2 gene. Genetic engineering techniques were used to modify the human IL-2 gene, and the resulting expression clone encodes a modified human interleukin-2. This recombinant form differs from native interleukin-2 in the following ways: a) aldesleukin is not glycosylated because it is derived from E. coli ; b) the molecule has no N-terminal alanine; the codon for this amino acid was deleted during the genetic engineering procedure; c) the molecule has serine substituted for cysteine at amino acid position 125; this was accomplished by site specific manipulation during the genetic engineering procedure; and d) the aggregation state of aldesleukin is likely to be different from that of native interleukin-2. The manufacturing process for aldesleukin involves fermentation in a defined medium containing tetracycline hydrochloride. The presence of the antibiotic is not detectable in the final product.

The in vitro biological activities of the native nonrecombinant molecule have been reproduced with aldesleukin.^1,2

Proleukin (aldesleukin) for injection is a sterile, preservative-free white to off-white, lyophilized powder, which has a cake-like appearance, supplied in single-dose vials for intravenous administration after reconstitution. When reconstituted with 1.2 mL Sterile Water for Injection, USP, each mL contains 18 million International Units (1.1 mg) aldesleukin, mannitol (50 mg), sodium dodecyl sulfate (0.19 mg), buffered with disodium hydrogen phosphate dihydrate (1.12 mg) and sodium dihydrogen phosphate dihydrate (0.19 mg) to a pH of 7.5 (range 7.2 to 7.8).

Proleukin biological potency is determined by a lymphocyte proliferation bioassay and is expressed in International Units as established by the World Health Organization 1st International Standard for Interleukin-2 (human). The relationship between potency and protein mass is as follows:

18 million International Units Proleukin = 1.1 mg protein

CLINICAL PHARMACOLOGY

Proleukin® (aldesleukin) has been shown to possess the biological activities of human native interleukin-2.^1,2 In vitro studies performed on human cell lines demonstrate the immunoregulatory properties of Proleukin, including: a) enhancement of lymphocyte mitogenesis and stimulation of long-term growth of human interleukin-2 dependent cell lines; b) enhancement of lymphocyte cytotoxicity; c) induction of killer cell (lymphokine-activated (LAK) and natural (NK)) activity; and d) induction of interferon-gamma production.

The in vivo administration of Proleukin in animals and humans produces multiple immunological effects in a dose dependent manner. These effects include activation of cellular immunity with profound lymphocytosis, eosinophilia, and thrombocytopenia, and the production of cytokines including tumor necrosis factor, IL-1 and gamma interferon. ^3 In vivo experiments in murine tumor models have shown inhibition of tumor growth.^4 The exact mechanism by which Proleukin mediates its antitumor activity in animals and humans is unknown.

Pharmacokinetics

Proleukin exists as biologically active, non-covalently bound microaggregates with an average size of 27 recombinant interleukin-2 molecules. The solubilizing agent, sodium dodecyl sulfate, may have an effect on the kinetic properties of this product.

The pharmacokinetic profile of Proleukin is characterized by high plasma concentrations following a short intravenous infusion, rapid distribution into the extravascular space and elimination from the body by metabolism in the kidneys with little or no bioactive protein excreted in the urine. Studies of intravenous Proleukin in sheep and humans indicate that upon completion of infusion, approximately 30% of the administered dose is detectable in plasma. This finding is consistent with studies in rats using radiolabeled Proleukin, which demonstrate a rapid (<1 min) uptake of the majority of the label into the lungs, liver, kidney, and spleen.

The serum half-life (T 1/2) curves of Proleukin remaining in the plasma are derived from studies done in 52 cancer patients following a 5-minute intravenous infusion. These patients were shown to have a distribution and elimination T 1/2 of 13 and 85 minutes, respectively.

Following the initial rapid organ distribution, the primary route of clearance of circulating Proleukin is the kidney. In humans and animals, Proleukin is cleared from the circulation by both glomerular filtration and peritubular extraction in the kidney.^5-8 This dual mechanism for delivery of Proleukin to the proximal tubule may account for the preservation of clearance in patients with rising serum creatinine values. Greater than 80% of the amount of Proleukin distributed to plasma, cleared from the circulation and presented to the kidney is metabolized to amino acids in the cells lining the proximal convoluted tubules. In humans, the mean clearance rate in cancer patients is 268 mL/min.

The relatively rapid clearance of Proleukin has led to dosage schedules characterized by frequent, short infusions. Observed serum levels are proportional to the dose of Proleukin.

CLINICAL STUDIES

Safety and efficacy were studied in a series of single and multicenter, historically controlled studies enrolling a total of 525 patients with metastatic renal cell carcinoma or melanoma. Eligible patients had an Eastern Cooperative Oncology Group (ECOG) Performance Status (PS) of 0 or 1 and normal organ function as determined by cardiac stress test, pulmonary function tests, and creatinine ≤1.5 mg/dL. Studies excluded patients with brain metastases, active infections, organ allografts and diseases requiring steroid treatment.

The same treatment dose and schedule was employed in all studies demonstrating efficacy. Proleukin was given by 15 min intravenous infusion every 8 hours for up to 5 days (maximum of 14 doses). No treatment was given on days 6 to 14 and then dosing was repeated for up to 5 days on days 15 to 19 (maximum of 14 doses). These 2 cycles constituted 1 course of therapy. Patients could receive a maximum of 28 doses during a course of therapy. In practice >90% of patients had doses withheld. Doses were withheld for specific toxicities (See “DOSAGE AND ADMINISTRATION” section, “Dose Modifications” subsection and “ADVERSE REACTIONS” section).

Metastatic Renal Cell Cancer

Two hundred fifty-five patients with metastatic renal cell cancer (metastatic RCC) were treated with single agent Proleukin in 7 clinical studies conducted at 21 institutions. Metastatic RCC patients received a median of 20 of 28 scheduled doses of Proleukin.

In the renal cell cancer studies (n=255), objective response was seen in 37 (15%) patients, with 17 (7%) complete and 20 (8%) partial responders (See Table 1). The 95% confidence interval for objective response was 11% to 20%. Onset of tumor regression was observed as early as 4 weeks after completion of the first course of treatment, and in some cases, tumor regression continued for up to 12 months after the start of treatment. Responses were observed in both lung and non-lung sites (e.g., liver, lymph node, renal bed occurrences, soft tissue). Responses were also observed in patients with individual bulky lesions and high tumor burden.

TABLE 1: Proleukin Clinical Response Data
 | Number of Responding Patients (response rate) | Median Response Duration in Months (range)
Metastatic RCC
CR’s | 17 (7%) | 80+* (7 to 131+)
PR’s | 20 (8%) | 20 (3 to 126+)
PR’s + CR’s | 37 (15%) | 54 (3 to 131+)

(+) sign means ongoing

* Median duration not yet observed; a conservative value is presented which represents the minimum median duration of response.

Lack of efficacy with low dose Proleukin regimens

Sixty-five patients with metastatic renal cell cancer were enrolled in a single center, open label, non-randomized trial that sequentially evaluated the safety and anti-tumor activity of two low dose Proleukin regimens. The regimens administered 18 million International Units Proleukin as a single subcutaneous injection, daily for 5 days during week 1; Proleukin was then administered at 9 x10^6 International Units days 1-2 and 18 x10^6 International Units days 3-5, weekly for an additional 3 weeks (n=40) followed by a 2 week rest or 5 weeks (n=25) followed by a 3 week rest, for a maximum of 3 or 2 treatment cycles, respectively.

These low dose regimens yielded substantially lower and less durable responses than those observed with the approved regimen. Based on the level of activity, these low dose regimens are not effective.

Metastatic Melanoma

Two hundred seventy patients with metastatic melanoma were treated with single agent Proleukin in 8 clinical studies conducted at 22 institutions. Metastatic melanoma patients received a median of 18 of 28 scheduled doses of Proleukin during the first course of therapy. In the metastatic melanoma studies (n=270), objective response was seen in 43 (16%) patients, with 17 (6%) complete and 26 (10%) partial responders (See Table 2). The 95% confidence interval for objective response was 12% to 21%. Responses in metastatic melanoma patients were observed in both visceral and non-visceral sites (e.g., lung, liver, lymph node, soft tissue, adrenal, subcutaneous). Responses were also observed in patients with individual bulky lesions and large cumulative tumor burden.

TABLE 2: Proleukin CLINICAL RESPONSE DATA
 | Number of Responding Patients (response rate) | Median Response Duration in Months (range)
Metastatic Melanoma
CR’s | 17 (6%) | 59+* (3 to 122+)
PR’s | 26 (10%) | 6 (1 to 111+)
PR’s + CR’s | 43 (16%) | 9 (1 to 122+)

(+) sign means ongoing

* Median duration not yet observed; a conservative value is presented which represents the minimum median duration of response.

INDICATIONS AND USAGE

Proleukin® (aldesleukin) is indicated for the treatment of adults with metastatic renal cell carcinoma (metastatic RCC).

Proleukin is indicated for the treatment of adults with metastatic melanoma.

Careful patient selection is mandatory prior to the administration of Proleukin. See “CONTRAINDICATIONS”, “WARNINGS” and “PRECAUTIONS” sections regarding patient screening, including recommended cardiac and pulmonary function tests and laboratory tests.

Evaluation of clinical studies to date reveals that patients with more favorable ECOG performance status (ECOG PS 0) at treatment initiation respond better to Proleukin, with a higher response rate and lower toxicity (See “CLINICAL PHARMACOLOGY” section, “CLINICAL STUDIES” section and “ADVERSE REACTIONS” section). Therefore, selection of patients for treatment should include assessment of performance status.

Experience in patients with ECOG PS >1 is extremely limited.

CONTRAINDICATIONS

Proleukin® (aldesleukin) is contraindicated in patients with a known history of hypersensitivity to interleukin-2 or any component of the Proleukin formulation.

Proleukin is contraindicated in patients with an abnormal thallium stress test or abnormal pulmonary function tests and those with organ allografts. Retreatment with Proleukin is contraindicated in patients who have experienced the following drug-related toxicities while receiving an earlier course of therapy:

• Sustained ventricular tachycardia (≥5 beats)

• Cardiac arrhythmias not controlled or unresponsive to management

• Chest pain with ECG changes, consistent with angina or myocardial infarction

• Cardiac tamponade

• Intubation for >72 hours

• Renal failure requiring dialysis >72 hours

• Coma or toxic psychosis lasting >48 hours

• Repetitive or difficult to control seizures

• Bowel ischemia/perforation

• GI bleeding requiring surgery

WARNINGS

See boxed “WARNINGS”

Because of the severe adverse events which generally accompany Proleukin® (aldesleukin) therapy at the recommended dosages, thorough clinical evaluation should be performed to identify patients with significant cardiac, pulmonary, renal, hepatic, or CNS impairment in whom Proleukin is contraindicated. Patients with normal cardiovascular, pulmonary, hepatic, and CNS function may experience serious, life threatening or fatal adverse events. Adverse events are frequent, often serious, and sometimes fatal.

Should adverse events, which require dose modification occur, dosage should be withheld rather than reduced (See “DOSAGE AND ADMINISTRATION” section, “Dose Modifications” subsection).

Proleukin has been associated with exacerbation of pre-existing or initial presentation of autoimmune disease and inflammatory disorders. Exacerbation of Crohn’s disease, scleroderma, thyroiditis, inflammatory arthritis, diabetes mellitus, oculo-bulbar myasthenia gravis, crescentic IgA glomerulonephritis, cholecystitis, cerebral vasculitis, Stevens-Johnson syndrome and bullous pemphigoid, has been reported following treatment with IL-2.

All patients should have thorough evaluation and treatment of CNS metastases and have a negative scan prior to receiving Proleukin therapy. New neurologic signs, symptoms, and anatomic lesions following Proleukin therapy have been reported in patients without evidence of CNS metastases. Clinical manifestations included changes in mental status, speech difficulties, cortical blindness, limb or gait ataxia, hallucinations, agitation, obtundation, and coma. Radiological findings included multiple and, less commonly, single cortical lesions on MRI and evidence of demyelination. Neurologic signs and symptoms associated with Proleukin therapy usually improve after discontinuation of Proleukin therapy; however, there are reports of permanent neurologic defects. One case of possible cerebral vasculitis, responsive to dexamethasone, has been reported. In patients with known seizure disorders, extreme caution should be exercised as Proleukin may cause seizures.

PRECAUTIONS

General

Patients should have normal cardiac, pulmonary, hepatic, and CNS function at the start of therapy. (See “PRECAUTIONS” section, “Laboratory Tests” subsection). Capillary leak syndrome (CLS) begins immediately after Proleukin® (aldesleukin) treatment starts and is marked by increased capillary permeability to protein and fluids and reduced vascular tone. In most patients, this results in a concomitant drop in mean arterial blood pressure within 2 to 12 hours after the start of treatment. With continued therapy, clinically significant hypotension (defined as systolic blood pressure below 90 mm Hg or a 20 mm Hg drop from baseline systolic pressure) and hypoperfusion will occur. In addition, extravasation of protein and fluids into the extravascular space will lead to the formation of edema and creation of new effusions.

Medical management of CLS begins with careful monitoring of the patient’s fluid and organ perfusion status. This is achieved by frequent determination of blood pressure and pulse, and by monitoring organ function, which includes assessment of mental status and urine output. Hypovolemia is assessed by catheterization and central pressure monitoring.

Flexibility in fluid and pressor management is essential for maintaining organ perfusion and blood pressure. Consequently, extreme caution should be used in treating patients with fixed requirements for large volumes of fluid (e.g., patients with hypercalcemia). Administration of IV fluids, either colloids or crystalloids is recommended for treatment of hypovolemia. Correction of hypovolemia may require large volumes of IV fluids but caution is required because unrestrained fluid administration may exacerbate problems associated with edema formation or effusions. With extravascular fluid accumulation, edema is common and ascites, pleural or pericardial effusions may develop. Management of these events depends on a careful balancing of the effects of fluid shifts so that neither the consequences of hypovolemia (e.g., impaired organ perfusion) nor the consequences of fluid accumulations (e.g., pulmonary edema) exceed the patient’s tolerance.

Clinical experience has shown that early administration of dopamine (1 to 5 mcg/kg/min) to patients manifesting capillary leak syndrome, before the onset of hypotension, can help to maintain organ perfusion particularly to the kidney and thus preserve urine output. Weight and urine output should be carefully monitored. If organ perfusion and blood pressure are not sustained by dopamine therapy, clinical investigators have increased the dose of dopamine to 6 to 10 mcg/kg/min or have added phenylephrine hydrochloride (1 to 5 mcg/kg/min) to low dose dopamine (See “ADVERSE REACTIONS” section). Prolonged use of pressors, either in combination or as individual agents, at relatively high doses, may be associated with cardiac rhythm disturbances. If there has been excessive weight gain or edema formation, particularly if associated with shortness of breath from pulmonary congestion, use of diuretics, once blood pressure has normalized, has been shown to hasten recovery. NOTE: Prior to the use of any product mentioned, the physician should refer to the package insert for the respective product.

Proleukin® (aldesleukin) treatment should be withheld for failure to maintain organ perfusion as demonstrated by altered mental status, reduced urine output, a fall in the systolic blood pressure below 90 mm Hg or onset of cardiac arrhythmias (See “DOSAGE AND ADMINISTRATION” section, “Dose Modifications” subsection). Recovery from CLS begins soon after cessation of Proleukin therapy. Usually, within a few hours, the blood pressure rises, organ perfusion is restored and reabsorption of extravasated fluid and protein begins.

Kidney and liver function are impaired during Proleukin treatment. Use of concomitant nephrotoxic or hepatotoxic medications may further increase toxicity to the kidney or liver.

Mental status changes including irritability, confusion, or depression which occur while receiving Proleukin may be indicators of bacteremia or early bacterial sepsis, hypoperfusion, occult CNS malignancy, or direct Proleukin-induced CNS toxicity. Alterations in mental status due solely to Proleukin therapy may progress for several days before recovery begins. Rarely, patients have sustained permanent neurologic deficits (See “PRECAUTIONS” section “Drug Interactions” subsection).

Exacerbation of pre-existing autoimmune disease or initial presentation of autoimmune and inflammatory disorders has been reported following Proleukin alone or in combination with interferon (See “PRECAUTIONS” section “Drug Interactions” subsection and “ADVERSE REACTIONS” section). Hypothyroidism, sometimes preceded by hyperthyroidism, has been reported following Proleukin treatment. Some of these patients required thyroid replacement therapy. Changes in thyroid function may be a manifestation of autoimmunity. Onset of symptomatic hyperglycemia and/or diabetes mellitus has been reported during Proleukin therapy.

Proleukin enhancement of cellular immune function may increase the risk of allograft rejection in transplant patients.

Serious manifestations of eosinophilia involving eosinophilic infiltration of cardiac and pulmonary tissues can occur following Proleukin.

Laboratory Tests

The following clinical evaluations are recommended for all patients, prior to beginning treatment and then daily during drug administration.

• Standard hematologic tests-including CBC, differential and platelet counts

• Blood chemistries-including electrolytes, renal and hepatic function tests

• Chest x-rays

Serum creatinine should be ≤1.5 mg/dL prior to initiation of Proleukin treatment.

All patients should have baseline pulmonary function tests with arterial blood gases. Adequate pulmonary function should be documented (FEV1 >2 liters or ≥75% of predicted for height and age) prior to initiating therapy.

All patients should be screened with a stress thallium study. Normal ejection fraction and unimpaired wall motion should be documented. If a thallium stress test suggests minor wall motion abnormalities further testing is suggested to exclude significant coronary artery disease.

Daily monitoring during therapy with Proleukin should include vital signs (temperature, pulse, blood pressure, and respiration rate), weight, and fluid intake and output. In a patient with a decreased systolic blood pressure, especially less than 90 mm Hg, constant cardiac rhythm monitoring should be conducted. If an abnormal complex or rhythm is seen, an ECG should be performed. Vital signs in these hypotensive patients should be taken hourly.

During treatment, pulmonary function should be monitored on a regular basis by clinical examination, assessment of vital signs and pulse oximetry. Patients with dyspnea or clinical signs of respiratory impairment (tachypnea or rales) should be further assessed with arterial blood gas determination. These tests are to be repeated as often as clinically indicated.

Cardiac function should be assessed daily by clinical examination and assessment of vital signs. Patients with signs or symptoms of chest pain, murmurs, gallops, irregular rhythm or palpitations should be further assessed with an ECG examination and cardiac enzyme evaluation. Evidence of myocardial injury, including findings compatible with myocardial infarction or myocarditis, has been reported. Ventricular hypokinesia due to myocarditis may be persistent for several months. If there is evidence of cardiac ischemia or congestive heart failure, Proleukin therapy should be held, and a repeat thallium study should be done.

Drug Interactions

Proleukin may affect central nervous function. Therefore, interactions could occur following concomitant administration of psychotropic drugs (e.g., narcotics, analgesics, antiemetics, sedatives, tranquilizers).

Concurrent administration of drugs possessing nephrotoxic (e.g., aminoglycosides, indomethacin), myelotoxic (e.g., cytotoxic chemotherapy), cardiotoxic (e.g., doxorubicin) or hepatotoxic (e.g., methotrexate, asparaginase) effects with Proleukin may increase toxicity in these organ systems. The safety and efficacy of Proleukin in combination with any antineoplastic agents have not been established.

In addition, reduced kidney and liver function secondary to Proleukin treatment may delay elimination of concomitant medications and increase the risk of adverse events from those drugs.

Hypersensitivity reactions have been reported in patients receiving combination regimens containing sequential high dose Proleukin and antineoplastic agents, specifically, dacarbazine, cis-platinum, tamoxifen and interferon-alfa. These reactions consisted of erythema, pruritus, and hypotension and occurred within hours of administration of chemotherapy. These events required medical intervention in some patients.

Myocardial injury, including myocardial infarction, myocarditis, ventricular hypokinesia, and severe rhabdomyolysis appear to be increased in patients receiving Proleukin and interferon-alfa concurrently.

Exacerbation or the initial presentation of a number of autoimmune and inflammatory disorders has been observed following concurrent use of interferon-alfa and Proleukin, including crescentic IgA glomerulonephritis, oculo-bulbar myasthenia gravis, inflammatory arthritis, thyroiditis, bullous pemphigoid, and Stevens-Johnson syndrome.

Although glucocorticoids have been shown to reduce Proleukin-induced side effects including fever, renal insufficiency, hyperbilirubinemia, confusion, and dyspnea, concomitant administration of these agents with Proleukin may reduce the antitumor effectiveness of Proleukin and thus should be avoided.^12

Beta-blockers and other antihypertensives may potentiate the hypotension seen with Proleukin.

Delayed Adverse Reactions to Iodinated Contrast Media

A review of the literature revealed that 12.6% (range 11-28%) of 501 patients treated with various interleukin-2 containing regimens who were subsequently administered radiographic iodinated contrast media experienced acute, atypical adverse reactions. The onset of symptoms usually occurred within hours (most commonly 1 to 4 hours) following the administration of contrast media. These reactions include fever, chills, nausea, vomiting, pruritus, rash, diarrhea, hypotension, edema, and oliguria. Some clinicians have noted that these reactions resemble the immediate side effects caused by interleukin-2 administration, however the cause of contrast reactions after interleukin-2 therapy is unknown. Most events were reported to occur when contrast media was given within 4 weeks after the last dose of interleukin-2. These events were also reported to occur when contrast media was given several months after interleukin-2 treatment.^13

Carcinogenesis, Mutagenesis, Impairment of Fertility

There have been no studies conducted assessing the carcinogenic or mutagenic potential of Proleukin.

There have been no studies conducted assessing the effect of Proleukin on fertility. It is recommended that this drug not be administered to fertile persons of either gender not practicing effective contraception.

Pregnancy

Pregnancy Category C.

Proleukin has been shown to have embryolethal effects in rats when given in doses at 27 to 36 times the human dose (scaled by body weight). Significant maternal toxicities were observed in pregnant rats administered Proleukin by IV injection at doses 2.1 to 36 times higher than the human dose during critical period of organogenesis. No evidence of teratogenicity was observed other than that attributed to maternal toxicity. There are no adequate well-controlled studies of Proleukin in pregnant women. Proleukin should be used during pregnancy only if the potential benefit justifies the potential risk to the fetus.

Nursing Mothers

It is not known whether this drug is excreted in human milk. Because many drugs are excreted in human milk and because of the potential for serious adverse reactions in nursing infants from Proleukin, a decision should be made whether to discontinue nursing or to discontinue the drug, taking into account the importance of the drug to the mother.

Pediatric Use

Safety and effectiveness in children under 18 years of age have not been established.

Geriatric Use

There were a small number of patients aged 65 and over in clinical trials of Proleukin; experience is limited to 27 patients, eight with metastatic melanoma and nineteen with metastatic renal cell carcinoma. The response rates were similar in patients 65 years and over as compared to those less than 65 years of age. The median number of courses and the median number of doses per course were similar between older and younger patients.

Proleukin is known to be substantially excreted by the kidney, and the risk of toxic reactions to this drug may be greater in patients with impaired renal function. The pattern of organ system toxicity and the proportion of patients with severe toxicities by organ system were generally similar in patients 65 and older and younger patients. There was a trend, however, towards an increased incidence of severe urogenital toxicities and dyspnea in the older patients.

ADVERSE REACTIONS

The rate of drug-related deaths in the 255 metastatic RCC patients who received single-agent Proleukin® (aldesleukin) was 4% (11/255); the rate of drug-related deaths in the 270 metastatic melanoma patients who received single-agent Proleukin was 2% (6/270).

The following data on common adverse events (reported in greater than 10% of patients, any grade), presented by body system, decreasing frequency and by preferred term (COSTART) are based on 525 patients (255 with renal cell cancer and 270 with metastatic melanoma) treated with the recommended infusion dosing regimen.

TABLE 3: ADVERSE EVENTS OCCURRING IN ≥10% OF PATIENTS (n=525)
Body System | % Patients | Body System | % Patients
Body as a Whole |  | Metabolic and Nutritional Disorders
Chills | 52 | Bilirubinemia | 40
Fever | 29 | Creatinine increase | 33
Malaise | 27 | Peripheral edema | 28
Asthenia | 23 | SGOT increase | 23
Infection | 13 | Weight gain | 16
Pain | 12 | Edema | 15
Abdominal pain | 11 | Acidosis | 12
Abdomen enlarged | 10 | Hypomagnesemia | 12
Cardiovascular |  | Hypocalcemia | 11
Hypotension | 71 | Alkaline phosphatase increase | 10
Tachycardia | 23 | Nervous
Vasodilation | 13 | Confusion | 34
Supraventricular tachycardia | 12 | Somnolence | 22
Cardiovascular disordera | 11 | Anxiety | 12
Arrhythmia | 10 | Dizziness | 11
Digestive |  | Respiratory
Diarrhea | 67 | Dyspnea | 43
Vomiting | 50 | Lung disorderb | 24
Nausea | 35 | Respiratory disorderc | 11
Stomatitis | 22 | Cough increase | 11
Anorexia | 20 | Rhinitis | 10
Nausea and vomiting | 19 | Skin and Appendages
Hemic and Lymphatic |  | Rash | 42
Thrombocytopenia | 37 | Pruritus | 24
Anemia | 29 | Exfoliative dermatitis | 18
Leukopenia | 16 | Urogenital
 |  | Oliguria | 63

a Cardiovascular disorder: fluctuations in blood pressure, asymptomatic ECG changes, CHF.

b Lung disorder: physical findings associated with pulmonary congestion, rales, rhonchi.

c Respiratory disorder: ARDS, CXR infiltrates, unspecified pulmonary changes.

The following data on life-threatening adverse events (reported in greater than 1% of patients, grade 4), presented by body system, and by preferred term (COSTART) are based on 525 patients (255 with renal cell cancer and 270 with metastatic melanoma) treated with the recommended infusion dosing regimen.

TABLE 4: LIFE-THREATENING (GRADE 4) ADVERSE EVENTS (n= 525)
Body System | # (%) Patients | Body System | # (%) Patients
Body as a Whole |  | Metabolic and Nutritional Disorders
Fever | 5 (1%) | Bilirubinemia | 13 (2%)
Infection | 7 (1%) | Creatinine increase | 5 (1%)
Sepsis | 6 (1%) | SGOT increase | 3 (1%)
Cardiovascular |  | Acidosis | 4 (1%)
Hypotension | 15 (3%) | Nervous
Supraventricular tachycardia | 3 (1%) | Confusion | 5 (1%)
Cardiovascular disordera | 7 (1%) | Stupor | 3 (1%)
Myocardial infarct | 7 (1%) | Coma | 8 (2%)
Ventricular tachycardia | 5 (1%) | Psychosis | 7 (1%)
Cardiac arrest | 4 (1%) | Respiratory
Digestive |  | Dyspnea | 5 (1%)
Diarrhea | 10 (2%) | Respiratory disorderc | 14 (3%)
Vomiting | 7 (1%) | Apnea | 5 (1%)
Hemic and Lymphatic |  | Urogenital
Thrombocytopenia | 5 (1%) | Oliguria | 33 (6%)
Coagulation disorderb | 4 (1%) | Anuria | 25 (5%)
 |  | Acute kidney failure | 3 (1%)

a Cardiovascular disorder: fluctuations in blood pressure.

b Coagulation disorder: intravascular coagulopathy.

c Respiratory disorder: ARDS, respiratory failure, intubation.

The following life-threatening (grade 4) events were reported by <1% of the 525 patients: hypothermia; shock; bradycardia; ventricular extrasystoles; myocardial ischemia; syncope; hemorrhage; atrial arrhythmia; phlebitis; AV block second degree; endocarditis; pericardial effusion; peripheral gangrene; thrombosis; coronary artery disorder; stomatitis; nausea and vomiting; liver function tests abnormal; gastrointestinal hemorrhage; hematemesis; bloody diarrhea; gastrointestinal disorder; intestinal perforation; pancreatitis; anemia; leukopenia; leukocytosis; hypocalcemia; alkaline phosphatase increase; BUN increase; hyperuricemia; NPN increase; respiratory acidosis; somnolence; agitation; neuropathy; paranoid reaction; convulsion; grand mal convulsion; delirium; asthma, lung edema; hyperventilation; hypoxia; hemoptysis; hypoventilation; pneumothorax; mydriasis; pupillary disorder; kidney function abnormal; kidney failure; acute tubular necrosis.

In an additional population of greater than 1,800 patients treated with Proleukin-based regimens using a variety of doses and schedules (e.g., subcutaneous, continuous infusion, administration with LAK cells) the following serious adverse events were reported: duodenal ulceration; bowel necrosis; myocarditis; supraventricular tachycardia; permanent or transient blindness secondary to optic neuritis; transient ischemic attacks; meningitis; cerebral edema; pericarditis; allergic interstitial nephritis; tracheo-esophageal fistula.

In the same clinical population, the following fatal events each occurred with a frequency of <1%: malignant hyperthermia; cardiac arrest; myocardial infarction; pulmonary emboli; stroke; intestinal perforation; liver or renal failure; severe depression leading to suicide; pulmonary edema; respiratory arrest; respiratory failure. In patients with both metastatic RCC and metastatic melanoma, those with ECOG PS of 1 or higher had a higher treatment-related mortality and serious adverse events.

Most adverse reactions are self-limiting and, usually, but not invariably, reverse or improve within 2 or 3 days of discontinuation of therapy. Examples of adverse reactions with permanent sequelae include: myocardial infarction, bowel perforation/infarction, and gangrene.

Immunogenicity

Serum samples from patients in the clinical studies were tested by enzyme-linked immunosorbent assay (ELISA) for anti-aldesleukin antibodies. Low titers of anti-aldesleukin antibodies were detected in 57 of 77 (74%) patients with metastatic renal cell carcinoma treated with an every 8-hour PROLEUKIN regimen and in 33 of 50 (66%) patients with metastatic melanoma treated with a variety of intravenous regimens. In a separate study, the effect of immunogenicity on the pharmacokinetics of aldesleukin was evaluated in 13 patients. Following the first cycle of therapy, comparing the geometric mean aldesleukin exposure (AUC) Day 15 to Day 1, there was an average 68% increase in 11 patients who developed anti-aldesleukin antibodies and no change was observed in the antibody-negative patients (n=2). Overall, neutralizing antibodies were detected in 1 patient. The impact of antialdesleukin antibody formation on clinical efficacy and safety of Proleukin is unknown.

Immunogenicity assay results are highly dependent on several factors including assay sensitivity and specificity, assay methodology, sample handling, timing of sample collection, concomitant medications, and underlying disease. For these reasons, comparison of incidence of antibodies to PROLEUKIN with the incidence of antibodies to other products may be misleading.

Post Marketing Experience

The following adverse reactions have been identified during post-approval use of Proleukin. Because these reactions are reported voluntarily from a population of uncertain size, it is not always possible to reliably estimate their frequency or establish a causal relationship to drug exposure.

- Blood and lymphatic system: neutropenia, febrile neutropenia, eosinophilia, lymphocytopenia
- Cardiac: cardiomyopathy, cardiac tamponade
- Endocrine: hyperthyroidism
- Gastrointestinal: gastritis, intestinal obstruction, colitis
- General and administration site conditions: injection site necrosis
- Hepatobiliary: hepatitis, hepatosplenomegaly, cholecystitis
- Immune system: anaphylaxis, angioedema, urticaria
- Infections and infestations: pneumonia (bacterial, fungal, viral), fatal endocarditis, cellulitis
- Musculoskeletal and connective tissue: myopathy, myositis, rhabdomyolysis
- Nervous system: cerebral lesions, encephalopathy, extrapyramidal syndrome, neuralgia, neuritis, demyelinating neuropathy
- Psychiatric: insomnia
- Vascular: hypertension, fatal subdural and subarachnoid hemorrhage, cerebral hemorrhage, retroperitoneal hemorrhage

Exacerbation or initial presentation of a number of autoimmune and inflammatory disorders have been reported (See “WARNINGS” section, “PRECAUTIONS” section, “Drug Interactions” subsection). Persistent but nonprogressive vitiligo has been observed in malignant melanoma patients treated with interleukin-2. Synergistic, additive and novel toxicities have been reported with Proleukin used in combination with other drugs. Novel toxicities include delayed adverse reactions to iodinated contrast media and hypersensitivity reactions to antineoplastic agents (See “PRECAUTIONS” section, “Drug Interactions” subsection).

Experience has shown the following concomitant medications to be useful in the management of patients on Proleukin therapy: a) standard antipyretic therapy, including nonsteroidal anti-inflammatories (NSAIDs), started immediately prior to Proleukin to reduce fever. Renal function should be monitored as some NSAIDs may cause synergistic nephrotoxicity; b) meperidine used to control the rigors associated with fever; c) H2 antagonists given for prophylaxis of gastrointestinal irritation and bleeding; d) antiemetics and antidiarrheals used as needed to treat other gastrointestinal side effects. Generally these medications were discontinued 12 hours after the last dose of Proleukin.

Patients with indwelling central lines have a higher risk of infection with gram positive organisms.^9-11 A reduced incidence of staphylococcal infections in Proleukin studies has been associated with the use of antibiotic prophylaxis which includes the use of oxacillin, nafcillin, ciprofloxacin, or vancomycin. Hydroxyzine or diphenhydramine has been used to control symptoms from pruritic rashes and continued until resolution of pruritus. Topical creams and ointments should be applied as needed for skin manifestations. Preparations containing a steroid (e.g., hydrocortisone) should be avoided. NOTE: Prior to the use of any product mentioned, the physician should refer to the package insert for the respective product.

OVERDOSAGE

Side effects following the use of Proleukin® (aldesleukin) appear to be dose-related. Exceeding the recommended dose has been associated with a more rapid onset of expected dose-limiting toxicities. Symptoms which persist after cessation of Proleukin should be monitored and treated supportively. Life-threatening toxicities may be ameliorated by the intravenous administration of dexamethasone, which may also result in loss of the therapeutic effects of Proleukin.^12 NOTE: Prior to the use of dexamethasone, the physician should refer to the package insert for this product.

DOSAGE AND ADMINISTRATION

The recommended Proleukin® (aldesleukin) treatment regimen is administered by a 15-minute intravenous infusion every 8 hours. Before initiating treatment, carefully review the “INDICATIONS AND USAGE”, “CONTRAINDICATIONS”, “WARNINGS”, “PRECAUTIONS”, and “ADVERSE REACTIONS” sections, particularly regarding patient selection, possible serious adverse events, patient monitoring and withholding dosage. The following schedule has been used to treat adult patients with metastatic renal cell carcinoma (metastatic RCC) or metastatic melanoma. Each course of treatment consists of two 5-day treatment cycles separated by a rest period.

600,000 International Units/kg (0.037 mg/kg) dose administered every 8 hours by a 15-minute intravenous infusion for a maximum of 14 doses. Following 9 days of rest, the schedule is repeated for another 14 doses, for a maximum of 28 doses per course, as tolerated. During clinical trials, doses were frequently withheld for toxicity (See “CLINICAL STUDIES” section and “Dose Modifications” subsection). Metastatic RCC patients treated with this schedule received a median of 20 of the 28 doses during the first course of therapy. Metastatic melanoma patients received a median of 18 doses during the first course of therapy.

Retreatment

Patients should be evaluated for response approximately 4 weeks after completion of a course of therapy and again immediately prior to the scheduled start of the next treatment course. Additional courses of treatment should be given to patients only if there is some tumor shrinkage following the last course and retreatment is not contraindicated (See “CONTRAINDICATIONS” section). Each treatment course should be separated by a rest period of at least 7 weeks from the date of hospital discharge.

Dose Modifications

Dose modification for toxicity should be accomplished by withholding or interrupting a dose rather than reducing the dose to be given. Decisions to stop, hold, or restart Proleukin therapy must be made after a global assessment of the patient. With this in mind, the following guidelines should be used:

Retreatment with Proleukin is contraindicated in patients who have experienced the following toxicities:

Body System

Cardiovascular

Sustained ventricular tachycardia (≥5 beats)

Cardiac rhythm disturbances not controlled or unresponsive to management

Chest pain with ECG changes, consistent with angina or myocardial infarction

Cardiac tamponade

Respiratory

Intubation for >72 hours

Urogenital

Renal failure requiring dialysis >72 hours

Nervous

Coma or toxic psychosis lasting >48 hours

Repetitive or difficult to control seizures

Digestive

Bowel ischemia/perforation

GI bleeding requiring surgery

Doses should be held and restarted according to the following:

Body System | Hold dose for | Subsequent doses may be given if
Cardiovascular | Atrial fibrillation, supraventricular tachycardia or bradycardia that requires treatment or is recurrent or persistent | Patient is asymptomatic with full recovery to normal sinus rhythm
 | Systolic bp <90 mm Hg with increasing requirements for pressors | Systolic bp ≥90 mm Hg and stable or improving requirements for pressors
 | Any ECG change consistent with MI, ischemia or myocarditis with or without chest pain; suspicion of cardiac ischemia | Patient is asymptomatic, MI and myocarditis have been ruled out, clinical suspicion of angina is low; there is no evidence of ventricular hypokinesia
Respiratory | O2 saturation <90% | O2 saturation >90%
Nervous | Mental status changes, including moderate confusion or agitation | Mental status changes completely resolved
Body as a Whole | Sepsis syndrome, patient is clinically unstable | Sepsis syndrome has resolved, patient is clinically stable, infection is under treatment
Urogenital | Serum creatinine >4.5 mg/dL or a serum creatinine of ≥4 mg/dL in the presence of severe volume overload, acidosis, or hyperkalemia | Serum creatinine <4 mg/dL and fluid and electrolyte status is stable
 | Persistent oliguria, urine output of <10 mL/hour for 16 to 24 hours with rising serum creatinine | Urine output >10 mL/hour with a decrease of serum creatinine >1.5 mg/dL or normalization of serum creatinine
Digestive | Signs of hepatic failure including encephalopathy, increasing ascites, liver pain, hypoglycemia | All signs of hepatic failure have resolved*
 | Stool guaiac repeatedly >3-4+ | Stool guaiac negative
Skin | Bullous dermatitis or marked worsening of pre-existing skin condition, avoid topical steroid therapy | Resolution of all signs of bullous dermatitis

* Discontinue all further treatment for that course. A new course of treatment, if warranted, should be initiated no sooner than 7 weeks after cessation of adverse event and hospital discharge.

Reconstitution and Dilution Directions: Reconstitution and dilution procedures other than those recommended may alter the delivery and/or pharmacology of Proleukin and thus should be avoided.

1. Proleukin® (aldesleukin) is a sterile, white to off-white, preservative-free, lyophilized powder suitable for IV infusion upon reconstitution and dilution. EACH VIAL CONTAINS 22 MILLION International Units (1.3 mg) OF PROLEUKIN AND SHOULD BE RECONSTITUTED ASEPTICALLY WITH 1.2 mL OF STERILE WATER FOR INJECTION, USP. WHEN RECONSTITUTED AS DIRECTED, EACH mL CONTAINS 18 MILLION International Units (1.1 mg) OF PROLEUKIN. The resulting solution should be a clear, colorless to slightly yellow liquid. The vial is for single-use only and any unused portion should be discarded.
2. During reconstitution, the Sterile Water for Injection, USP should be directed at the side of the vial and the contents gently swirled to avoid excess foaming. DO NOT SHAKE.
3. The dose of Proleukin, reconstituted with Sterile Water for Injection, USP (without preservative) should be diluted aseptically in 50 mL of 5% Dextrose Injection, USP (D5W) and infused over a 15-minute period.
  In cases where the total dose of Proleukin is 1.5 mg or less (e.g., a patient with a body weight of less than 40 kilograms), the dose of Proleukin should be diluted in a smaller volume of D5W. Concentrations of Proleukin below 0.03 mg/mL and above 0.07 mg/mL have shown increased variability in drug delivery. Dilution and delivery of Proleukin outside of this concentration range should be avoided.
4. Glass bottles and plastic (polyvinyl chloride) bags have been used in clinical trials with comparable results. It is recommended that plastic bags be used as the dilution container since experimental studies suggest that use of plastic containers results in more consistent drug delivery. In-line filters should not be used when administering Proleukin.
5. Before and after reconstitution and dilution, store in a refrigerator at 2° to 8°C (36° to 46°F). Do not freeze. Administer Proleukin within 48 hours of reconstitution. The solution should be brought to room temperature prior to infusion in the patient.
6. Reconstitution or dilution with Bacteriostatic Water for Injection, USP, or 0.9% Sodium Chloride Injection, USP should be avoided because of increased aggregation. Proleukin should not be coadministered with other drugs in the same container.
7. Parenteral drug products should be inspected visually for particulate matter and discoloration prior to administration, whenever solution and container permit.

HOW SUPPLIED

Proleukin® (aldesleukin) is supplied in individually boxed single-dose vials. Each vial contains 22 million International Units of Proleukin. Discard unused portion.

NDC 65483-116-07 Individually boxed single-dose vial

Store vials of lyophilized Proleukin in a refrigerator at 2° to 8°C (36° to 46°F). PROTECT FROM LIGHT. Store in carton until time of use.

Reconstituted or diluted Proleukin is stable for up to 48 hours at refrigerated and room temperatures, 2° to 25°C (36° to 77°F). However, since this product contains no preservative, the reconstituted and diluted solutions should be stored in the refrigerator.

Do not use beyond the expiration date printed on the vial. NOTE: This product contains no preservative.

Rx Only

REFERENCES

1. Doyle MV, Lee MT, Fong S. Comparison of the biological activities of human recombinant interleukin-2^125 and native interleukin-2. J Biol Response Mod 1985; 4:96-109.
2. Ralph P, Nakoinz I, Doyle M, et al. Human B and T lymphocyte stimulating properties of interleukin-2 (IL-2) muteins. In: Immune Regulation By Characterized Polypeptides. Alan R. Liss, Inc. 1987; 453-62.
3. Winkelhake JL and Gauny SS. Human recombinant interleukin-2 as an experimental therapeutic. Pharmacol Rev 1990; 42:1-28.
4. Rosenberg SA, Mule JJ, Spiess PJ, et al. Regression of established pulmonary metastases and subcutaneous tumor mediated by the systemic administration of high-dose recombinant interleukin-2. J Exp Med 1985; 161:1169-88.
5. Konrad MW, Hemstreet G, Hersh EM, et al. Pharmacokinetics of recombinant interleukin-2 in humans. Cancer Res 1990; 50:2009-17.
6. Donohue JH and Rosenberg SA. The fate of interleukin-2 after in vivo administration. J Immunol 1983; 130:2203-8.
7. Koths K, Halenbeck R. Pharmacokinetic studies on ^35S-labeled recombinant interleukin-2 in mice. In: Sorg C and Schimpl A, eds. Cellular and Molecular Biology of Lymphokines. Academic Press: Orlando, FL, 1985;779.
8. Gibbons JA, Luo ZP, Hansen ER, et al. Quantitation of the renal clearance of interleukin-2 using nephrectomized and ureter ligated rats. J Pharmacol Exp Ther 1995; 272: 119-125.
9. Bock SN, Lee RE, Fisher B, et al. A prospective randomized trial evaluating prophylactic antibiotics to prevent triple-lumen catheter-related sepsis in patients treated with immunotherapy. J Clin Oncol 1990; 8:161-69.
10. Hartman LC, Urba WJ, Steis RG, et al. Use of prophylactic antibiotics for prevention of intravascular catheter-related infections in interleukin-2-treated patients. J Natl Cancer Inst 1989; 81:1190-93.
11. Snydman DR, Sullivan B, Gill M, et al. Nosocomial sepsis associated with interleukin-2. Ann Intern Med 1990; 112:102-07.
12. Mier JW, Vachino G, Klempner MS, et al. Inhibition of interleukin-2-induced tumor necrosis factor release by dexamethasone: Prevention of an acquired neutrophil chemotaxis defect and differential suppression of interleukin-2 associated side effects. Blood 1990; 76:1933-40.
13. Choyke PL, Miller DL, Lotze MT, et al. Delayed reactions to contrast media after interleukin-2 immunotherapy. Radiology 1992; 183:111-114.

Manufactured by:

Prometheus Laboratories Inc.

San Diego, CA 92121

U.S. License No. 1848

At

Boehringer Ingelheim Pharma

Biberach/Riss, Germany

For additional information, contact Prometheus Laboratories Inc. 1-877-PROLEUKIN (1-877-776-5385)

PROLEUKIN is a registered trademark of Novartis Vaccines and Diagnostics, Inc.

© 2010-2018 Prometheus Laboratories Inc.

PROMETHEUS®
Therapeutics & Diagnostics

REV: May 2019 PR001J

Principal Display Panel - Proleukin Label

NDC 65483-116-07 Rx only

Proleukin®

(aldesleukin)

for injection, for intravenous infusion

22 million International Units/Vial (1.3mg/vial)

Single-Use Vial Discard Unused Portion

Principal Display Panel - Proleukin Carton

NDC 65483-116-07

Proleukin®

(aldesleukin)

for injection,

for intravenous infusion

22 million

International Units/Vial

(1.3 mg/vial)

Single-Use Vial

Discard Unused Portion

For Intravenous Use Only

Refrigerate

Rx only